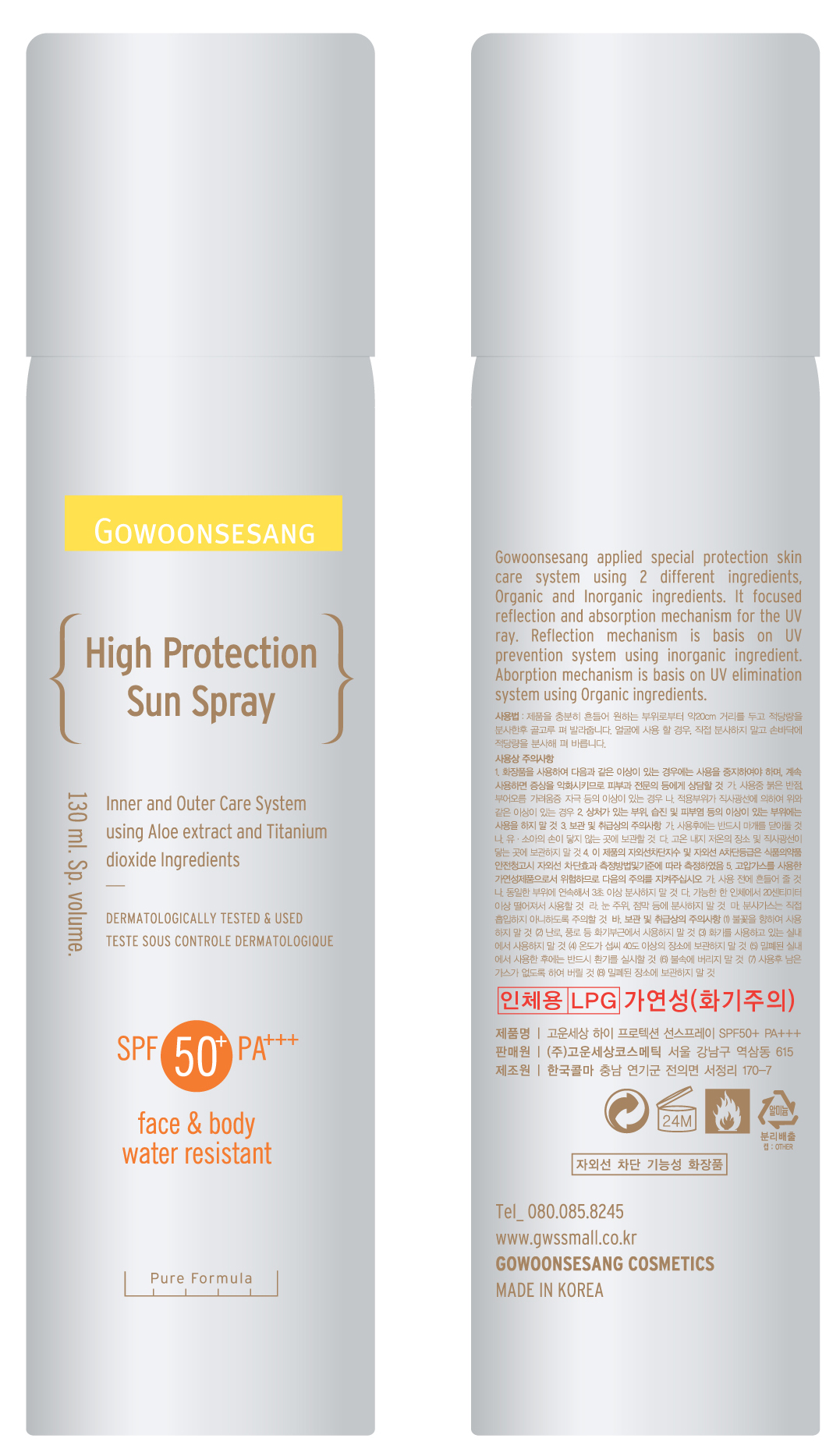 DRUG LABEL: High Protection Sun Air Spray SPF50 PA
NDC: 43948-6001 | Form: SPRAY
Manufacturer: The Doctor's Cosmetic Inc
Category: otc | Type: HUMAN OTC DRUG LABEL
Date: 20091001

ACTIVE INGREDIENTS: OCTINOXATE 9.75 mL/130 mL
INACTIVE INGREDIENTS: OCTISALATE; ALUMINUM HYDROXIDE

INACTIVE INGREDIENTS:

Water, Cyclopentasiloxane, Ethylhexyl Methosycinnamate, Alcohol, Zinc Oxide, Ethylhexyl Salicylate, Isodecyl Neopentanoate, Butylene Glycol, Titanium Dioxide, Peg-10 Dimethicone, Methyl Methacrylate Crosspolymer, Methicone, Aluminum Stearate, Aluminum Hydroxide, Sodium Chloride, Fragrance, Calcium Aluminum Borosilicate, Imidazolidinyl Urea, Polyglyceryl-6 Polyricinoleate, Sodium Hyaluronate, Rosemarinus Officinalis (Rosemary) Leaf Extract, Opuntia Ficus - Indica Extract, Chamomilla Recutita (Matricaria) Flower Extract, Aloe Barbadensis Leaf Juice, Methylparaben, Propylparaben, Butylparaben

CAUTION: Keep away from children.

WHEN USING

DIRECTION OF USE:

Apply 15-30 minutes before sun exposure. Do not apply in windy conditions. Hold can 4-6 inches away from body and apply liberally, spraying slowly and evenly until product is visible on skin. Spray into hand and apply to the face. Use in well ventilated areas. Reapply after swimming, excessive perspiration, towel drying or extended sun exposure.

PACKAGE LABEL

Label16c